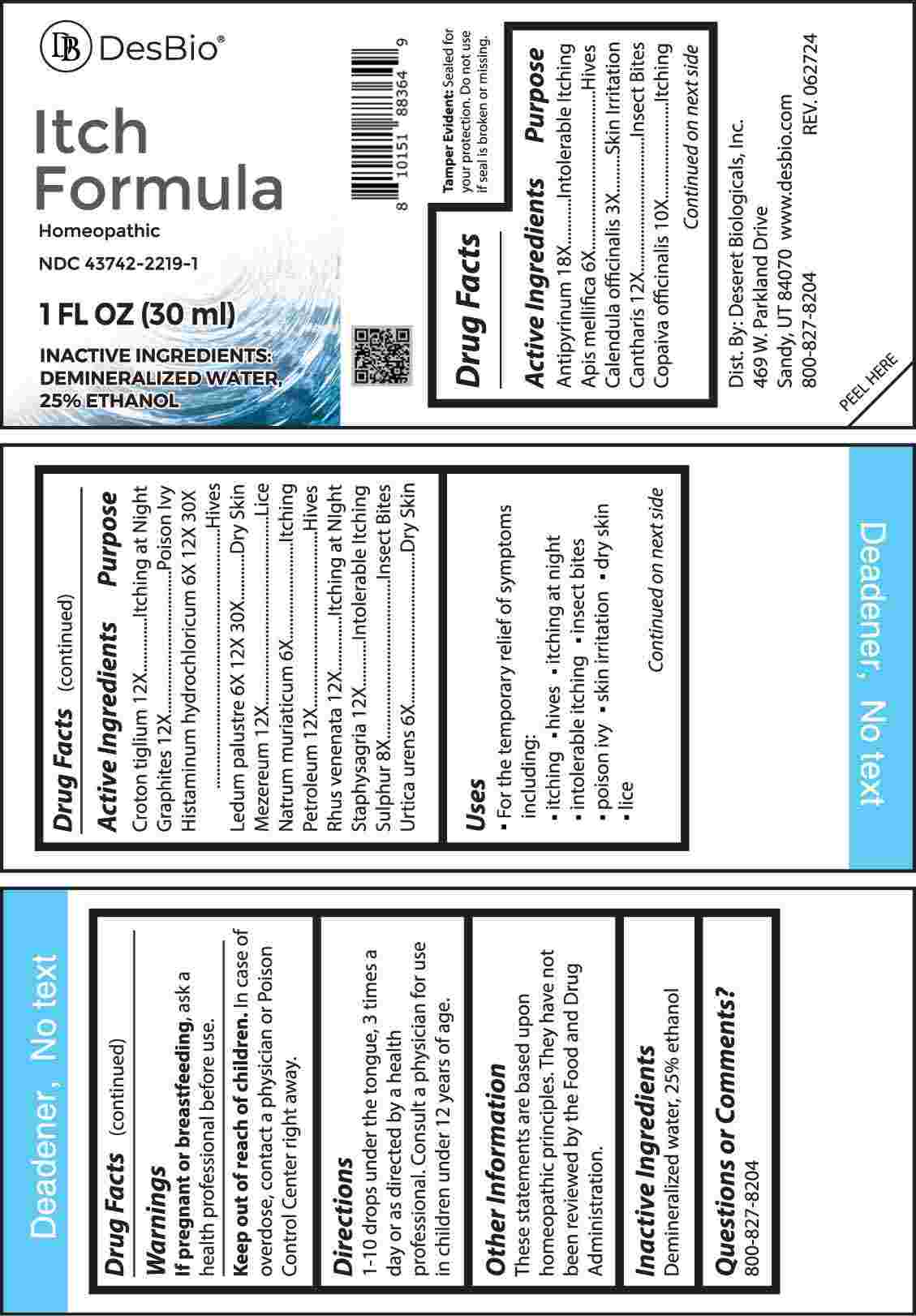 DRUG LABEL: Itch Formula
NDC: 43742-2219 | Form: LIQUID
Manufacturer: Deseret Biologicals, Inc.
Category: homeopathic | Type: HUMAN OTC DRUG LABEL
Date: 20241112

ACTIVE INGREDIENTS: ANTIPYRINE 18 [hp_X]/1 mL; APIS MELLIFERA 6 [hp_X]/1 mL; CALENDULA OFFICINALIS FLOWERING TOP 3 [hp_X]/1 mL; LYTTA VESICATORIA 12 [hp_X]/1 mL; COPAIFERA OFFICINALIS RESIN 10 [hp_X]/1 mL; CROTON TIGLIUM SEED 12 [hp_X]/1 mL; GRAPHITE 12 [hp_Q]/1 mL; HISTAMINE DIHYDROCHLORIDE 6 [hp_X]/1 mL; RHODODENDRON TOMENTOSUM LEAFY TWIG 6 [hp_X]/1 mL; DAPHNE MEZEREUM BARK 12 [hp_X]/1 mL; SODIUM CHLORIDE 6 [hp_X]/1 mL; KEROSENE 12 [hp_X]/1 mL; TOXICODENDRON VERNIX LEAFY TWIG 12 [hp_X]/1 mL; DELPHINIUM STAPHISAGRIA SEED 12 [hp_X]/1 mL; SULFUR 8 [hp_X]/1 mL; URTICA URENS WHOLE 6 [hp_X]/1 mL
INACTIVE INGREDIENTS: WATER; ALCOHOL

DRUG FACTS:

ACTIVE INGREDIENTS:

Antipyrinum 18X, Apis Mellifica 6X, Calendula Officinalis 3X, Cantharis 12X, Copaiva Officinalis 10X, Croton Tiglium 12X, Graphites 12X, Histaminum Hydrochloricum 6X, 12X, 30X, Ledum Palustre 6X, 12X, 30X, Mezereum 12X, Natrum Muriaticum 6X, Petroleum 12X, Rhus Venenata 12X, Staphysagria 12X, Sulphur 8X, Urtica Urens 6X.

PURPOSE:

Antipyrinum – Intolerable Itching, Apis Mellifica - Hives, Calendula Officinalis – Skin Irritation, Cantharis – Insect Bites, Copaiva Officinalis - Itching, Croton Tiglium – Itching at Night, Graphites – Poison Ivy, Histaminum Hydrochloricum - Hives, Ledum Palustre – Dry Skin, Mezereum - Lice, Natrum Muriaticum - Itching, Petroleum - Hives, Rhus Venenata – Itching at Night, Staphysagria – Intolerable Itching, Sulphur – Insect Bites, Urtica Urens – Dry Skin

USES:

• For the temporary relief of symptoms including:

• itching • hives • itching at night • intolerable itching

• insect bites • poison ivy • skin irritation • dry skin • lice

These statements are based upon homeopathic principles. They have not been reviewed by the Food and Drug Administration.

WARNINGS:

If pregnant or breast-feeding, ask a health professional before use.

Keep out of reach of children. In case of overdose, contact a physician or Poison Control Center right away.

Tamper Evident: Sealed for your protection. Do not use if seal is broken or missing.

KEEP OUT OF REACH OF CHILDREN:

In case of overdose, contact a physician or Poison Control Center right away.

DIRECTIONS:

1-10 drops under the tongue, 3 times a day or as directed by a health professional. Consult a physician for use in children under 12 years of age.

INACTIVE INGREDIENTS:

Demineralized water, 25% ethanol

QUESTIONS:

Dist. By: Deseret Biologicals, Inc.

469 W. Parkland Drive

Sandy, UT 84070

www.desbio.com

800-827-8204

PACKAGE LABEL DISPLAY:

DesBio

Itch Formula

Homeopathic

NDC 43742-2219-1

1 FL OZ (30 ml)